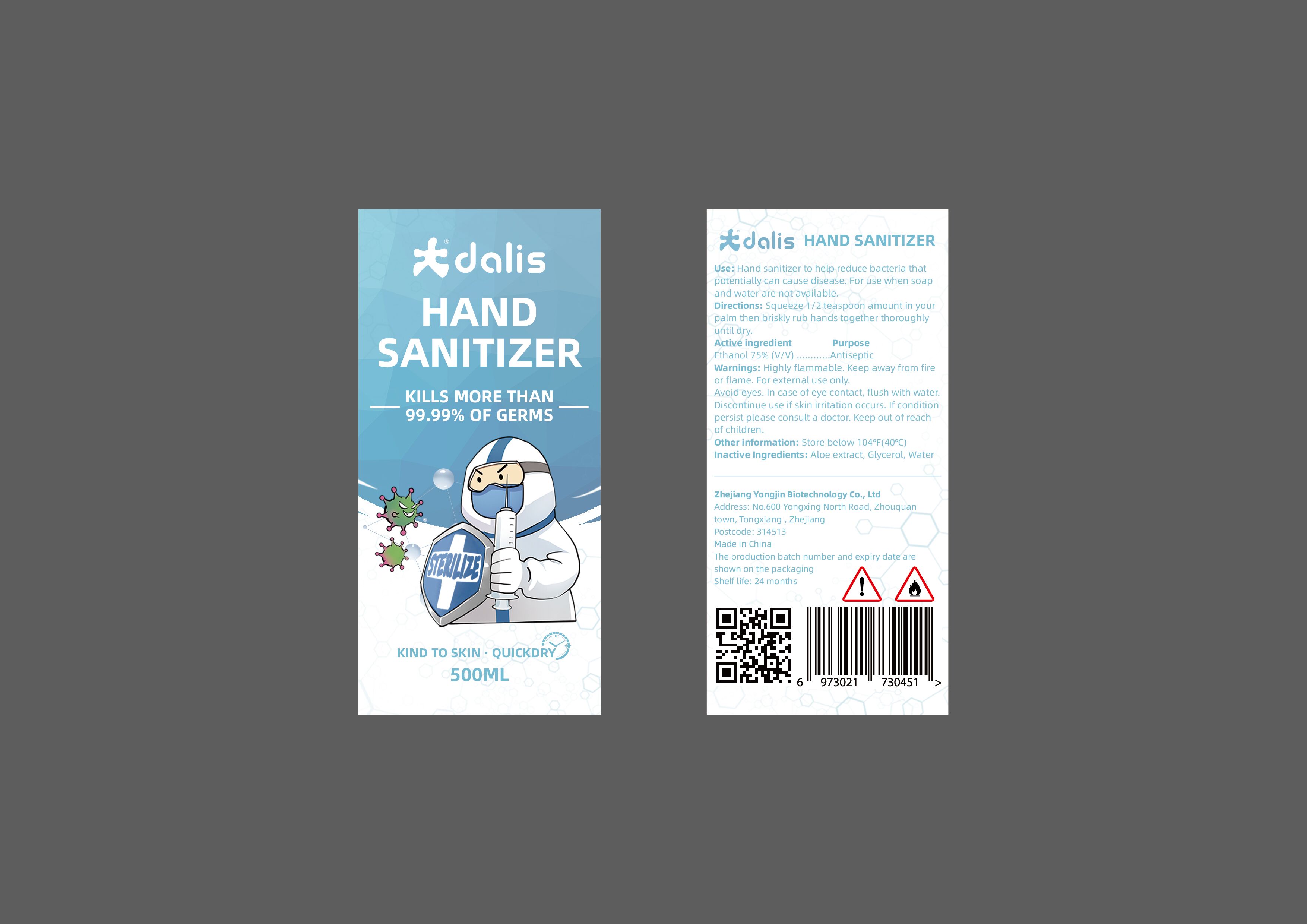 DRUG LABEL: Dalis HAND SANITIZER
NDC: 77639-001 | Form: SOLUTION
Manufacturer: Zhejiang Yongjin Biotechnology Co., Ltd
Category: otc | Type: HUMAN OTC DRUG LABEL
Date: 20200512

ACTIVE INGREDIENTS: ALCOHOL 75 mL/100 mL
INACTIVE INGREDIENTS: GLYCEROL FORMAL; WATER; ALOE

Active Ingredient(s)

Ethanol 75%

Purpose

Antiseptic

Use

Hand sanitizer to help reduce bacteria that potentially can cause disease

For use when soap and water are not available

Warnings

For external use only -hands

Highly flammable. Keep away from fire or flame

Avoid eyes. In case of eye contact, flush with water

STOP USE

Discontinue if skin irritation occurs. If condition persists, please consult a doctor.

Keep out of reach of children.

Directions

- Squeeze 1/2 tea spoon amount in you plam then briskly rub hands together thoroughly until dry

Other information

Store below 104F (40C)

Inactive ingredients

Water, glycerol, aloe extract